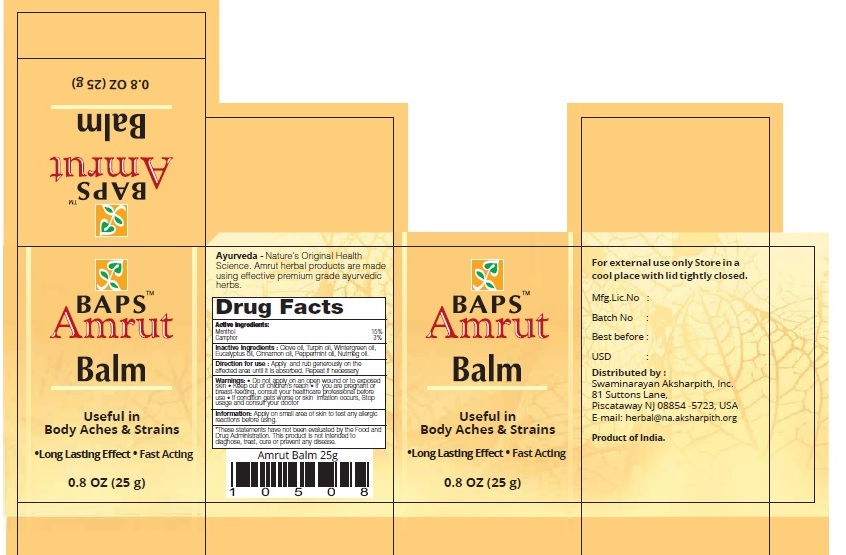 DRUG LABEL: Amrut Balm
NDC: 57631-105 | Form: OINTMENT
Manufacturer: InvaTech Pharma Solutions LLC
Category: otc | Type: HUMAN OTC DRUG LABEL
Date: 20170623

ACTIVE INGREDIENTS: MENTHOL 3.7 g/1 g; CAMPHOR (NATURAL) 0.75 g/1 g
INACTIVE INGREDIENTS: CLOVE OIL; TURNIP-ROOTED CHERVIL OIL; EUCALYPTUS OIL; CINNAMON OIL; PEPPERMINT OIL; NUTMEG OIL

BAPS AMRUT BALM

BAPS AMRUT BALM Active Ingredeints

Menthol 15%

Camphor 3%

Purpose

Menthol Topical analgesic

Camphor Topical analgesic

Uses

Useful in Body Aches & Strains

Long Lasting Effect
Fast Acting

Inactive Ingredients

- Clove oil
- Turpin oil
- Wintergreen oil
- Eucalyptus oil
- Cinnamon oil
- Peppermint oil
- Nutmeg oil

Directions for use

Apply and rub generously on the affected area until it is absorbed. Repeat if necessary

Warnings

For external use only

- Do not apply on an open wound or to exposed skin
- If you are pregnant or breast-feeding, consult your healthcare professional before use
- If condition gets worse or skin irritation occurs, stop usage and consult your doctor

Keep out of children's reach

Other Information

Apply on small area of skin to test any allergic reactions before using.

(*These statements have not been evaluated by the Food and Drug Administration. This product is not intended to diagnose, treat, cure or prevent any disease.)